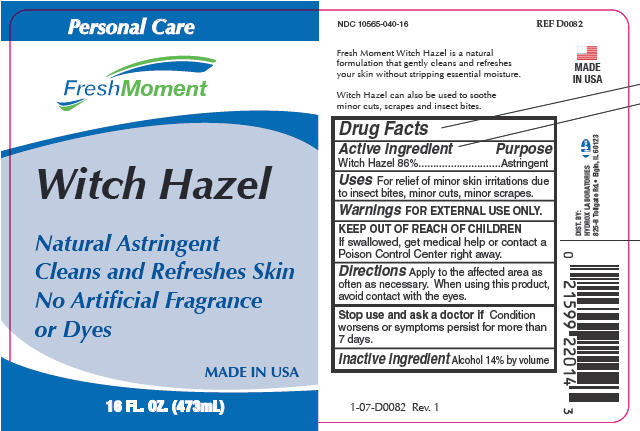 DRUG LABEL: Witch Hazel
NDC: 10565-040 | Form: LIQUID
Manufacturer: Hydrox Laboratories
Category: otc | Type: HUMAN OTC DRUG LABEL
Date: 20260112

ACTIVE INGREDIENTS: WITCH HAZEL 86 g/100 mL
INACTIVE INGREDIENTS: ALCOHOL

Witch Hazel

Drug Facts

Active ingredient

Witch Hazel 86%

Purpose

Astringent

Uses

For relief of minor skin irritations due to insect bites, minor cuts, minor scrapes.

Warnings

FOR EXTERNAL USE ONLY.

KEEP OUT OF REACH OF CHILDREN

If swallowed, get medical help or contact a Poison Control Center right away.

Directions

Apply to the affected area as often as necessary. When using this product, avoid contact with the eyes.

Stop use and ask a doctor ifCondition worsens or symptoms persist for more than 7 days.

Inactive ingredient

Alcohol 14% by volume

DIST. BY:
HYDROX LABORATORIES
825-B Tollgate Rd.• Elgin, IL 60123

PRINCIPAL DISPLAY PANEL - 473 mL Bottle Label

Personal Care

FreshMoment

Witch Hazel

Natural Astringent
Cleans and Refreshes Skin
No Artificial Fragrance
or Dyes

MADE IN USA

16 FL. OZ. (473mL)